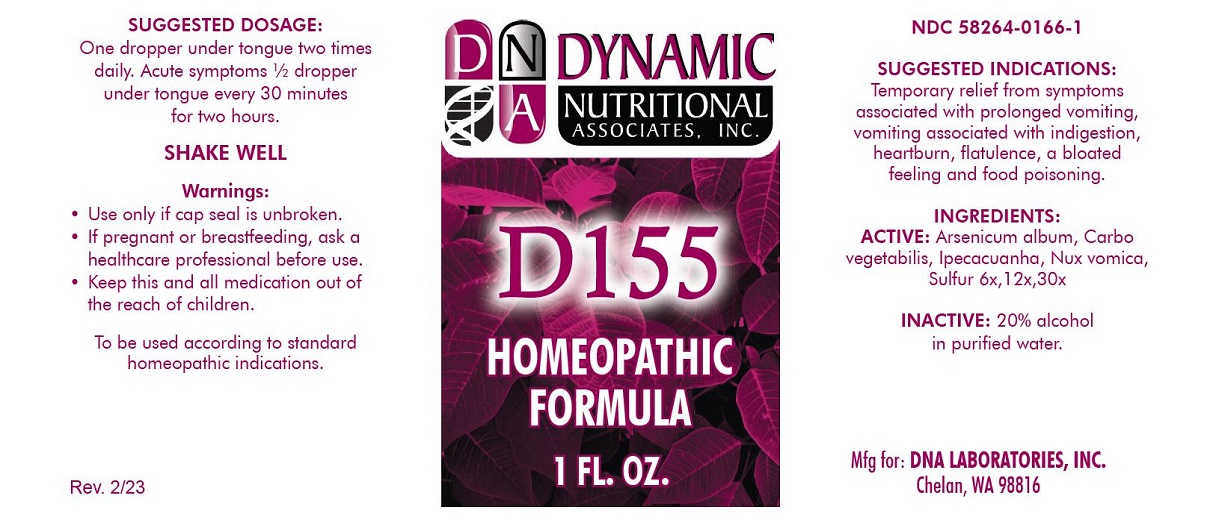 DRUG LABEL: D-155
NDC: 58264-0166 | Form: SOLUTION
Manufacturer: DNA Labs
Category: homeopathic | Type: HUMAN OTC DRUG LABEL
Date: 20250113

ACTIVE INGREDIENTS: ARSENIC TRIOXIDE 30 [hp_X]/1 mL; STRYCHNOS NUX-VOMICA SEED 30 [hp_X]/1 mL; ACTIVATED CHARCOAL 30 [hp_X]/1 mL; IPECAC 30 [hp_X]/1 mL
INACTIVE INGREDIENTS: WATER; ALCOHOL

D-155

NDC 58264-0166-1

INDICATIONS AND USAGE

PURPOSE

Temporary relief from symptoms associated with prolonged vomiting, vomiting associated with indigestion, heartburn, flatulence, a bloated feeling and food poisoning.

INGREDIENTS

ACTIVE

Arsenicum album, Carbo vegetabilis, Ipecacuanha, Nux vomica, Sulfur 6x,12x,30x

INACTIVE

20% alcohol in purified water.

SUGGESTED DOSAGE

One dropper under tongue two times daily. Acute symptoms ½ dropper under tongue every 30 minutes for two hours.

STORAGE AND HANDLING

SHAKE WELL

WARNINGS

- Use only if cap seal is unbroken.

PREGNANCY OR BREAST FEEDING

- If pregnant or breastfeeding, ask a healthcare professional before use.

KEEP OUT OF REACH OF CHILDREN

- Keep this and all medication out of the reach of children.

To be used according to standard homeopathic indications.

PRINCIPAL DISPLAY PANEL - 1 FL. OZ. - Bottle Label

DYNAMIC

NUTRITIONAL

ASSOCIATES, INC.

D-155

HOMEOPATHIC

1 FL. OZ.